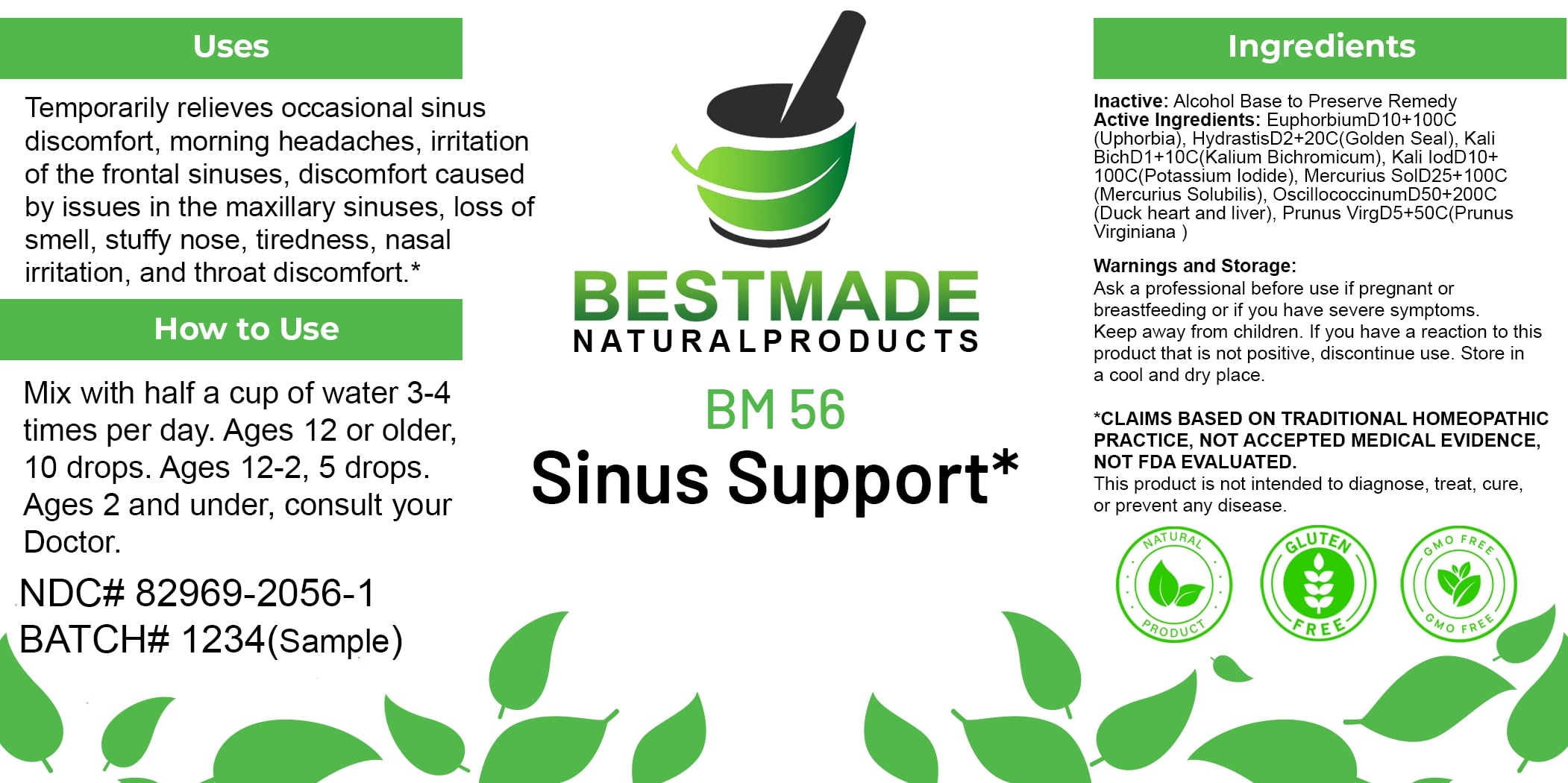 DRUG LABEL: Bestmade Natural Products BM56
NDC: 82969-2056 | Form: LIQUID
Manufacturer: Bestmade Natural Products
Category: homeopathic | Type: HUMAN OTC DRUG LABEL
Date: 20250124

ACTIVE INGREDIENTS: MERCURIUS SOLUBILIS 100 [hp_C]/200 [hp_C]; EUPHORBIA RESINIFERA RESIN 100 [hp_C]/200 [hp_C]; GOLDENSEAL 20 [hp_C]/200 [hp_C]; POTASSIUM IODIDE 100 [hp_C]/200 [hp_C]; POTASSIUM DICHROMATE 10 [hp_C]/200 [hp_C]; PRUNUS SEROTINA BARK 50 [hp_C]/200 [hp_C]; CAIRINA MOSCHATA HEART/LIVER AUTOLYSATE 200 [hp_C]/200 [hp_C]
INACTIVE INGREDIENTS: ALCOHOL 200 [hp_C]/200 [hp_C]

BM56

DOSAGE AND ADMINISTRATION

How to Use

Mix with half a cup of water 3-4 times per day. Ages 12 or older, 10 drops. Ages 12-2, 5 drops. Ages 2 and under, consult your Doctor.

INACTIVE INGREDIENT

Ingredients

Inactive: Alcohol Base to Preserve Remedy

ACTIVE INGREDIENT

Active Ingredients: Euphorbium D10+100C (Euphorbia), Hydrastis D2+20C (Golden Seal), Kali Bich D1+10C (Kalium Bichromicum), Kali Iod D10+100C (Potassium Iodide), Mercurius Sol D25+100C (Mercurius Solubilis), Oscillococcinum D50+200C (Duck heart and liver), Prunus Virg D5+50C (Prunus Virginiana)

Uses

Temporarily relieves occasional sinus discomfort, morning headaches, irritation of the frontal sinuses, discomfort caused by issues in the maxillary sinuses, loss of smell, stuffy nose, tiredness, nasal irritation, and throat discomfort.*

*CLAIMS BASED ON TRADITIONAL HOMEOPATHIC PRACTICE, NOT ACCEPTED MEDICAL EVIDENCE. NOT FDA EVALUATED.

This product is not intended to diagnose, treat, cure, or prevent any disease.

Uses

Temporarily relieves occasional sinus discomfort, morning headaches, irritation of the frontal sinuses, discomfort caused by issues in the maxillary sinuses, loss of smell, stuffy nose, tiredness, nasal irritation, and throat discomfort.*

*CLAIMS BASED ON TRADITIONAL HOMEOPATHIC PRACTICE, NOT ACCEPTED MEDICAL EVIDENCE. NOT FDA EVALUATED.

This product is not intended to diagnose, treat, cure, or prevent any disease.

KEEP OUT OF REACH OF CHILDREN

Warnings and Storage:

Ask a professional before use if pregnant or breastfeeding or if you have severe symptoms. Keep away from children. If you have a reaction to this product that is not positive, discontinue use. Store in a cool and dry place.

Warnings and Storage:

Ask a professional before use if pregnant or breastfeeding or if you have severe symptoms. Keep away from children. If you have a reaction to this product that is not positive, discontinue use. Store in a cool and dry place.

*CLAIMS BASED ON TRADITIONAL HOMEOPATHIC PRACTICE, NOT ACCEPTED MEDICAL EVIDENCE. NOT FDA EVALUATED.

This product is not intended to diagnose, treat, cure, or prevent any disease.

Entire package label